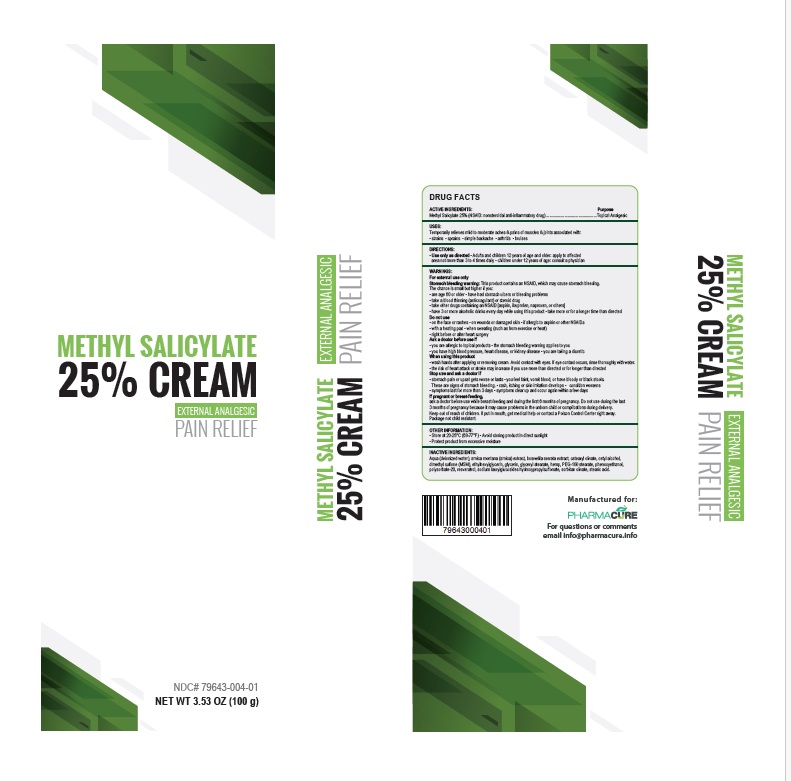 DRUG LABEL: Methyl Salicylate
NDC: 79643-004 | Form: CREAM
Manufacturer: PHARMACURE LLC
Category: otc | Type: HUMAN OTC DRUG LABEL
Date: 20251006

ACTIVE INGREDIENTS: METHYL SALICYLATE 250 mg/1 g
INACTIVE INGREDIENTS: WATER; ARNICA MONTANA FLOWER; INDIAN FRANKINCENSE; CETEARYL OLIVATE; CETYL ALCOHOL; DIMETHYL SULFONE; ETHYLHEXYLGLYCERIN; GLYCERIN; GLYCERYL MONOSTEARATE; HEMP; PEG-100 STEARATE; PHENOXYETHANOL; POLYSORBATE 20; RESVERATROL; SODIUM LAURYLGLUCOSIDES HYDROXYPROPYLSULFONATE; SORBITAN OLIVATE; STEARIC ACID

Active Ingredient Purpose

Methyl Salicylate 25% (NSAID: Nonsteroidal anti-inflammatory drug) Topical Analgesic

Uses

Temporarily relieves mild to moderate aches & pains of muscles & joints associated with:

• strains • sprains • simple backache • arthritis • bruises

Warnings

For external use only
Stomach bleeding warning: This product contains an NSAID, which may cause stomach bleeding.
The chance is small but higher if you:

• are age 60 or older • have had stomach ulcers or bleeding problems
• take a blood thinning (anticoagulant) or steroid drug
• take other drugs containing an NSAID (aspirin, ibuprofen, naproxen, or others]
• have 3 or more alcoholic drinks every day while using this product • take more or for a longer time than directed

Do not use

• on the face or rashes • on wounds or damaged skin • if allergic to aspirin or other NSAIDs
• with a heating pad • when sweating (such as from exercise or heat)
• right before or after heart surgery

Ask a doctor before use if
• you are allergic to topical products • the stomach bleeding warning applies to you
• you have high blood pressure, heart disease, or kidney disease • you are taking a diuretic

When using this product

• wash hands after applying or removing patch. Avoid contact with eyes. If eye contact occurs, rinse thoroughly with water.
• the risk of heart attack or stroke may increase if you use more than directed or for longer than directed

Stop use and ask a doctor if
• stomach pain or upset gets worse or lasts • you feel faint, vomit blood, or have bloody or black stools
These are signs of stomach bleeding. • rash, itching or skin irritation develops
• condition worsens
• symptoms last for more than 3 days • symptoms clear up and occur again within a few days

If pregnant or breast-feeding,

ask a doctor before use while breast-feeding and during the first 6 months of pregnancy. Do not use during the last 3 months of pregnancy because it may cause problems in the unborn child or complications during delivery.
Keep out of reach of children. If put in mouth, get medical help or contact a Poison Control Center right away. Package not child resistant. Dispose of the used patches after folding sticky ends together.

Directions

• Use only as directed
• Adults and children 12 years of age and older: Apply to affected area not more than 3 to 4 times daily •children under 12 years of age: consult a physician

Other information

• Store at 20-25°C (68-77°F) • Avoid storing product in direct sunlight
•Protect product from excessive moisture

Inactive ingredients

Aqua (deionized water), arnica montana (arnica) extract, boswellia serrata extract, cetearyl olivate, cetyl alcohol, dimethyl sulfone (MSM), ethylhexylglycerin, glycerin, glyceryl stearate, hemp, PEG-100 stearate, phenoxyethanol, polysorbate-20, resveratrol, sodium laurylglucosides hydroxypropylsulfonate, sorbital olivate, stearic acid